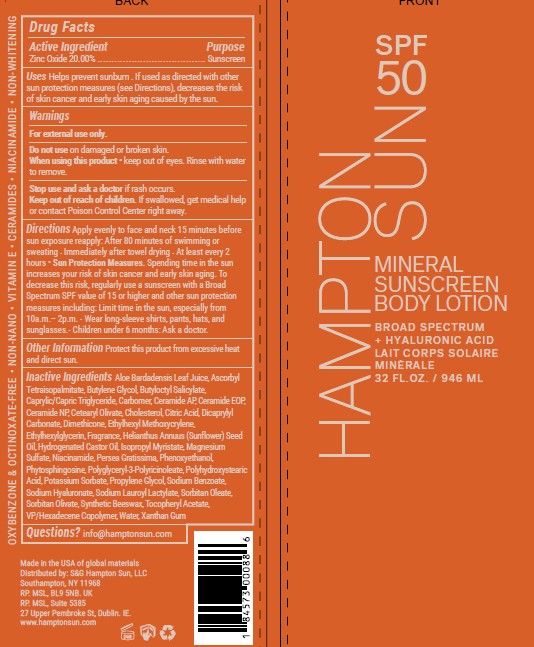 DRUG LABEL: Zinc Oxide 20%
NDC: 87170-006 | Form: LOTION
Manufacturer: S&C Hampton Sun
Category: otc | Type: HUMAN OTC DRUG LABEL
Date: 20260127

ACTIVE INGREDIENTS: ZINC OXIDE 20 g/100 mL
INACTIVE INGREDIENTS: ALOE BARBADENSIS LEAF JUICE; ASCORBYL TETRAISOPALMITATE; BUTYLENE GLYCOL; BUTYLOCTYL SALICYLATE; MEDIUM-CHAIN TRIGLYCERIDES; CARBOMER; CERAMIDE AP; CERAMIDE 9; CERAMIDE NP; CETEARYL OLIVATE; CHOLESTEROL; CITRIC ACID; DICAPRYLYL CARBONATE; DIMETHICONE; ETHYLHEXYL METHOXYCRYLENE; ETHYLHEXYLGLYCERIN; HELIANTHUS ANNUUS (SUNFLOWER) SEED OIL; CASTOR OIL; ISOPROPYL MYRISTATE; MAGNESIUM SULFATE, UNSPECIFIED FORM; NIACINAMIDE; PERSEA GRATISSIMA (AVOCADO) OIL; PHENOXYETHANOL; PHYTOSPHINGOSINE; POLYHYDROXYSTEARIC ACID (2300 MW); POTASSIUM SORBATE; PROPYLENE GLYCOL; SODIUM BENZOATE; SODIUM HYALURONATE; SODIUM LAUROYL LACTYLATE; SORBITAN OLEATE; SORBITAN OLIVATE; SYNTHETIC BEESWAX; .ALPHA.-TOCOPHEROL ACETATE; VP/HEXADECENE COPOLYMER; WATER

Hampton Sun SPF 50 Mineral Lotion

Uses

Helps prevent sunburn . If used as directed with other
sun protection measures (see Directions), decreases the risk
of skin cancer and early skin aging caused by the sun.

Directions

Apply evenly to face and neck 15 minutes before sun
exposure reapply: After 80 minutes of swimming or sweating .
Immediately after towel drying . At least every 2 hours • Sun Protection
Measures.Spending time in the sun increases your risk of skin cancer
and early skin aging. To decrease this risk, regularly use a sunscreen
with a Broad Spectrum SPF value of 15 or higher and other sun
protection measures including: Limit time in the sun, especially from
10a.m.– 2p.m. . Wear long-sleeve shirts, pants, hats, and sunglasses.
. Children under 6 months: Ask a doctor.

Warnings For external use only.

Do not useon damaged or broken skin.
When using this product• keep out of eyes. Rinse with water to remove.
Stop use and ask a doctor ifrash occurs.

Keep out of reach of children.

If swallowed, get medical help or contact Poison Control Center right away

Inactive ingredients

Aloe Barbadensis Leaf Juice
Ascorbyl Tetraisopalmitate
Butylene Glycol
Butyloctyl Salicylate
Caprylic/Capric Triglyceride
Carbomer
Ceramide AP
Ceramide EOP
Ceramide NP
Cetearyl Olivate
Cholesterol
Citric Acid
Dicaprylyl Carbonate
Dimethicone
Ethylhexyl Methoxycrylene
Ethylhexylglycerin
Fragrance
Helianthus Annuus (Sunflower) Seed Oil
Hydrogenated Castor Oil
Isopropyl Myristate
Magnesium Sulfate
Niacinamide
Persea Gratissima
Phenoxyethanol
Phytosphingosine
Polyglyceryl-3 Polyricinoleate
Polyhydroxystearic Acid
Potassium Sorbate
Propylene Glycol
Sodium Benzoate
Sodium Hyaluronate
Sodium Lauroyl Lactylate
Sorbitan Oleate
Sorbitan Olivate
Synthetic Beeswax
Tocopheryl Acetate
VP/Hexadecene Copolymer
Water
Xanthan Gum